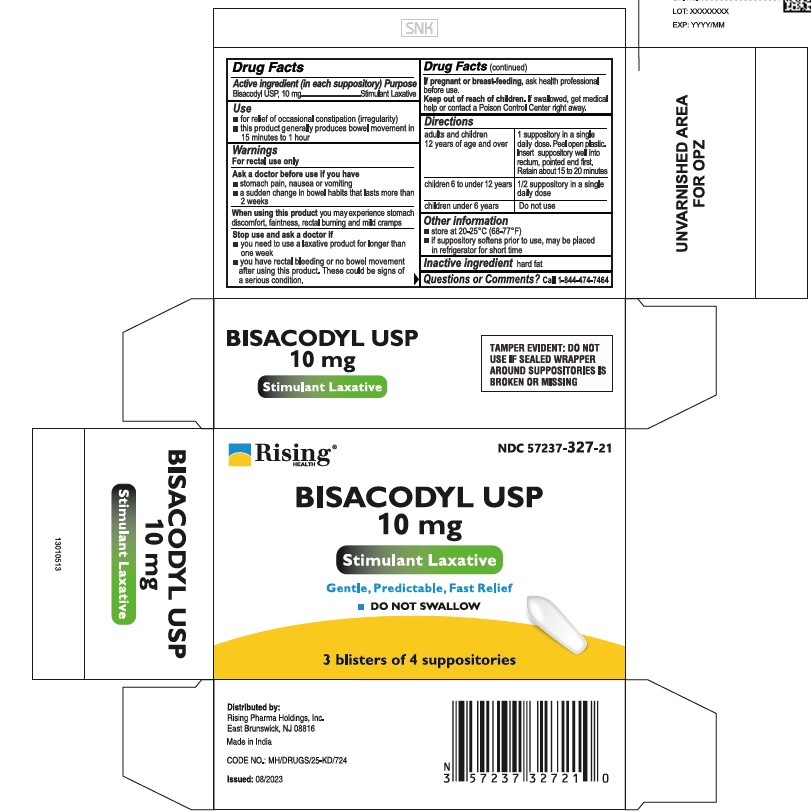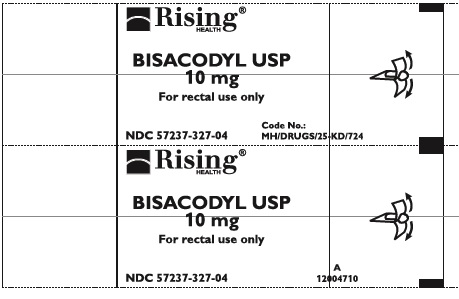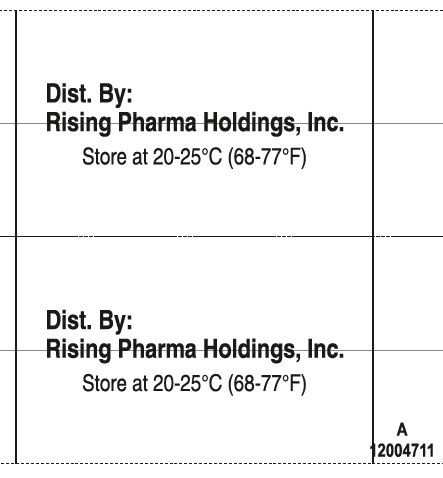 DRUG LABEL: Bisacodyl
NDC: 57237-327 | Form: SUPPOSITORY
Manufacturer: Rising Pharma Holdings, Inc.
Category: otc | Type: HUMAN OTC DRUG LABEL
Date: 20250513

ACTIVE INGREDIENTS: BISACODYL 10 mg/1 1
INACTIVE INGREDIENTS: FAT, HARD

Bisacodyl USP Suppositories 10 mg

Drug Facts

Active ingredient (in each suppository)

Bisacodyl USP, 10 mg

Purpose

Stimulant Laxative

Use

- for relief of occasional constipation (irregularity)
- this product generally produces bowel movement in 15 minutes to 1 hour

Warnings

For rectal use only

Ask a doctor before use if you have

- stomach pain, nausea or vomiting
- a sudden change in bowel habits that lasts more than 2 weeks

When using this product you may experience stomach discomfort, faintness, rectal burning and mild cramps

Stop use and ask a doctor if

- you need to use a laxative product for longer than one week
- you have rectal bleeding or no bowel movement after using this product. These could be signs of a serious condition.

PREGNANCY OR BREAST FEEDING

If pregnant or breast-feeding, ask health professional before use.

Keep out of reach of children. If swallowed, get medical help or contact a Poison Control Center right away.

Directions

adults and children; 12 years of age and over | 1 suppository in a single daily dose. Peel open plastic. Insert suppository; well into rectum, pointed end first. Retain about 15 to 20 minutes
children 6 to under 12 years | 1/2 suppository in a single daily dose
children under 6 years | Do not use

Other information

- store at 20-25°C (68-77°F)
- if suppository softens prior to use, may be placed in refrigerator for short time

Inactive ingredient hard fat

Questions or Comments? Call 1-844-474-7464

OTHER SAFETY INFORMATION

TAMPER EVIDENT: DO NOT USE IF SEALED WRAPPER AROUND SUPPOSITORIES IS BROKEN OR MISSING

Distributed by:
Rising Pharma Holdings, Inc.
East Brunswick, NJ 08816

Made in India

CODE NO.: MH/DRUGS/25-KD/724

Issued: 08/2023

PACKAGE LABEL

NDC 57237-327-21 (3 blisters of 4 suppositories)

Bisacodyl USP Suppositories 10 mg

Stimulant Laxative

Gentle, Predictable, Fast Relief

DO NOT SWALLOW

NDC 57237-327-04 (4 suppositories in 1 blister pack)

Front Foil

Back Foil